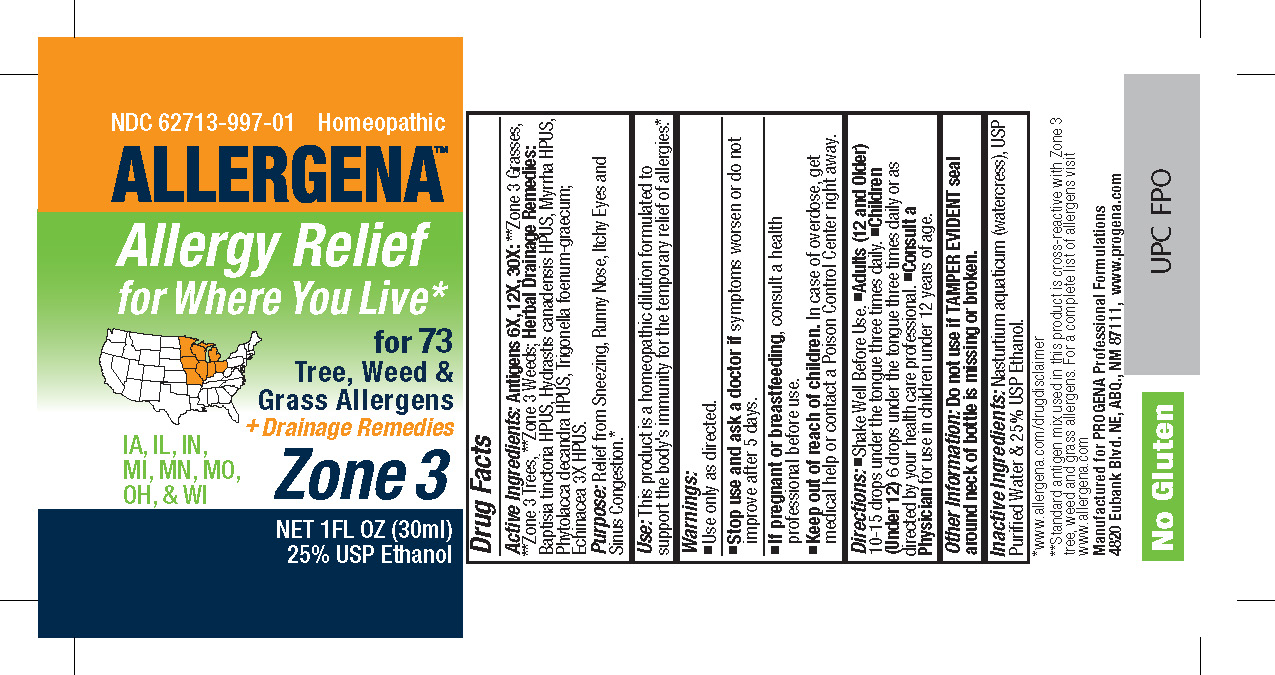 DRUG LABEL: Allergena Zone 3

NDC: 62713-997 | Form: LIQUID
Manufacturer: Meditrend, Inc. DBA Progena Professional Formulations
Category: homeopathic | Type: HUMAN OTC DRUG LABEL
Date: 20250130

ACTIVE INGREDIENTS: ECHINACEA, UNSPECIFIED 3 [hp_X]/1 mL; BAPTISIA TINCTORIA ROOT 3 [hp_X]/1 mL; GOLDENSEAL 3 [hp_X]/1 mL; MYRRH 3 [hp_X]/1 mL; PHYTOLACCA AMERICANA ROOT 3 [hp_X]/1 mL; FENUGREEK LEAF 3 [hp_X]/1 mL; ALNUS INCANA SUBSP. RUGOSA POLLEN 30 [hp_X]/1 mL; FRAXINUS VELUTINA POLLEN 30 [hp_X]/1 mL; FRAXINUS PENNSYLVANICA POLLEN 30 [hp_X]/1 mL; FRAXINUS AMERICANA POLLEN 30 [hp_X]/1 mL; POPULUS TREMULOIDES POLLEN 30 [hp_X]/1 mL; FAGUS GRANDIFOLIA POLLEN 30 [hp_X]/1 mL; BETULA OCCIDENTALIS POLLEN 30 [hp_X]/1 mL; BETULA PAPYRIFERA POLLEN 30 [hp_X]/1 mL; ACER NEGUNDO POLLEN 30 [hp_X]/1 mL; JUNIPERUS ASHEI POLLEN 30 [hp_X]/1 mL; JUNIPERUS VIRGINIANA POLLEN 30 [hp_X]/1 mL; POPULUS DELTOIDES POLLEN 30 [hp_X]/1 mL; ULMUS AMERICANA POLLEN 30 [hp_X]/1 mL; ULMUS PUMILA POLLEN 30 [hp_X]/1 mL; CELTIS OCCIDENTALIS POLLEN 30 [hp_X]/1 mL; CARYA TOMENTOSA POLLEN 30 [hp_X]/1 mL; ACER SACCHARUM POLLEN 30 [hp_X]/1 mL; MORUS RUBRA POLLEN 30 [hp_X]/1 mL; MORUS ALBA POLLEN 30 [hp_X]/1 mL; QUERCUS VELUTINA POLLEN 30 [hp_X]/1 mL; QUERCUS MACROCARPA POLLEN 30 [hp_X]/1 mL; QUERCUS STELLATA POLLEN 30 [hp_X]/1 mL; QUERCUS ALBA POLLEN 30 [hp_X]/1 mL; CARYA ILLINOINENSIS POLLEN 30 [hp_X]/1 mL; PINUS STROBUS POLLEN 30 [hp_X]/1 mL; POPULUS NIGRA POLLEN 30 [hp_X]/1 mL; POPULUS ALBA POLLEN 30 [hp_X]/1 mL; LIGUSTRUM VULGARE POLLEN 30 [hp_X]/1 mL; LIQUIDAMBAR STYRACIFLUA POLLEN 30 [hp_X]/1 mL; PLATANUS OCCIDENTALIS POLLEN 30 [hp_X]/1 mL; AILANTHUS ALTISSIMA POLLEN 30 [hp_X]/1 mL; JUGLANS NIGRA POLLEN 30 [hp_X]/1 mL; SALIX NIGRA POLLEN 30 [hp_X]/1 mL; AMPHIACHYRIS DRACUNCULOIDES POLLEN 30 [hp_X]/1 mL; AMARANTHUS PALMERI POLLEN 30 [hp_X]/1 mL; XANTHIUM STRUMARIUM POLLEN 30 [hp_X]/1 mL; RUMEX CRISPUS POLLEN 30 [hp_X]/1 mL; SOLIDAGO CANADENSIS POLLEN 30 [hp_X]/1 mL; CHENOPODIUM ALBUM POLLEN 30 [hp_X]/1 mL; IVA ANNUA POLLEN 30 [hp_X]/1 mL; CHENOPODIUM AMBROSIOIDES POLLEN 30 [hp_X]/1 mL; URTICA DIOICA POLLEN 30 [hp_X]/1 mL; AMARANTHUS RETROFLEXUS POLLEN 30 [hp_X]/1 mL; AMARANTHUS SPINOSUS POLLEN 30 [hp_X]/1 mL; PLANTAGO LANCEOLATA POLLEN 30 [hp_X]/1 mL; AMBROSIA TRIFIDA POLLEN 30 [hp_X]/1 mL; AMBROSIA ARTEMISIIFOLIA POLLEN 30 [hp_X]/1 mL; AMBROSIA PSILOSTACHYA POLLEN 30 [hp_X]/1 mL; ARTEMISIA TRIDENTATA POLLEN 30 [hp_X]/1 mL; ARTEMISIA LUDOVICIANA POLLEN 30 [hp_X]/1 mL; RUMEX ACETOSELLA POLLEN 30 [hp_X]/1 mL; AMARANTHUS TUBERCULATUS POLLEN 30 [hp_X]/1 mL; ARTEMISIA ANNUA POLLEN 30 [hp_X]/1 mL; ARTEMISIA ABSINTHIUM POLLEN 30 [hp_X]/1 mL; CYNODON DACTYLON POLLEN 30 [hp_X]/1 mL; POA ANNUA POLLEN 30 [hp_X]/1 mL; BROMUS INERMIS POLLEN 30 [hp_X]/1 mL; PHALARIS ARUNDINACEA POLLEN 30 [hp_X]/1 mL; ZEA MAYS POLLEN 30 [hp_X]/1 mL; SORGHUM HALEPENSE POLLEN 30 [hp_X]/1 mL; KOELERIA MACRANTHA POLLEN 30 [hp_X]/1 mL; POA PRATENSIS POLLEN 30 [hp_X]/1 mL; FESTUCA PRATENSIS POLLEN 30 [hp_X]/1 mL; AVENA SATIVA POLLEN 30 [hp_X]/1 mL; DACTYLIS GLOMERATA POLLEN 30 [hp_X]/1 mL; LOLIUM MULTIFLORUM POLLEN 30 [hp_X]/1 mL; LOLIUM PERENNE POLLEN 30 [hp_X]/1 mL; SORGHUM BICOLOR POLLEN 30 [hp_X]/1 mL; TRITICUM AESTIVUM POLLEN 30 [hp_X]/1 mL; PASCOPYRUM SMITHII POLLEN 30 [hp_X]/1 mL
INACTIVE INGREDIENTS: WATER; ALCOHOL; NASTURTIUM OFFICINALE

Allergena Zone 3

ACTIVE INGREDIENT

Active Ingredients:Echinacea 3X HPUS; Drainage Remedies:Baptisia tinctoria 3X HPUS, Hydrastis canadensis 3X HPUS, Myrrha 3X HPUS, Nasturtium aquaticum 3X HPUS, Phytolacca decandra 3X HPUS, Trigonella foenum-graecum 3X; *Zone 3 Tree 6X, 12X, 30X: *Zone 3 Weed 6X, 12X, 30X: *Zone 3 Grass 6X, 12X, 30X.

ACTIVE INGREDIENT

Active Ingredients: Antigens 6X, 12X, 30X:**Zone 3 Grasses, **Zone 3 Trees, **Zone 3 Weeds; Herbal Drainage Remedies 3X:Baptisia tinctoria HPUS, Hydrastis canadensis HPUS, Myrrha HPUS, Phytolacca decandra HPUS, Trigonella foenum-graecum; Echinacea 3X HPUS.

PURPOSE

Purpose:Relief from Sneezing, Runny Nose, Itchy Eyes and Sinus Congestion.*

INDICATIONS AND USAGE

Use:This product is a Homeopathic Dilution formulated to support the body's immunity for the temporary relief of allergies.*

Keep Out of Reach of Children.In case of overdose, get medical help or contact a
Poison Control Center right away.

Warnings:

- Use Only as directed.
- Stop use and ask a doctorif symptoms worsen or do not improve after 5 days.
- If pregnant or breast-feeding, consult a health professional before use.

DOSAGE AND ADMINISTRATION

Directions:•Shake Well Before Use. • Adults (12 and Older)10-15 drops under the tongue three times daily. • Children (2-12) 6-10 drops under the tongue three times daily. • Infants (0-2)3-6 drops under the tongue three times daily or as directed by your health care professional.

Other Information: Do not use if TAMPER EVIDENT seal around neck of bottle is missing or broken.

INACTIVE INGREDIENT

Inactive Ingredients:Nasturtium aquaticum (watercress), USP Purified Water and 25% UPS Ethanol.

PACKAGE LABEL

*www.allergena.com/drugdisclaimer
**Standard antigen mix used in this product is cross-reactive with Zone 3 Tree, Weed, and Grass allergens. For a complete list of allergens visit
www.allergena.com

Manufactured for PROGENA Professional Formulations
4820 Eubank Blvd. NE, ABQ, NM 87111, www.progena.com